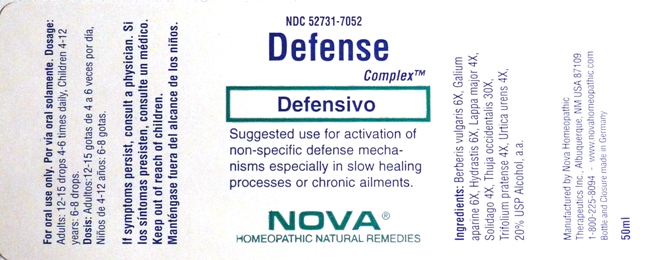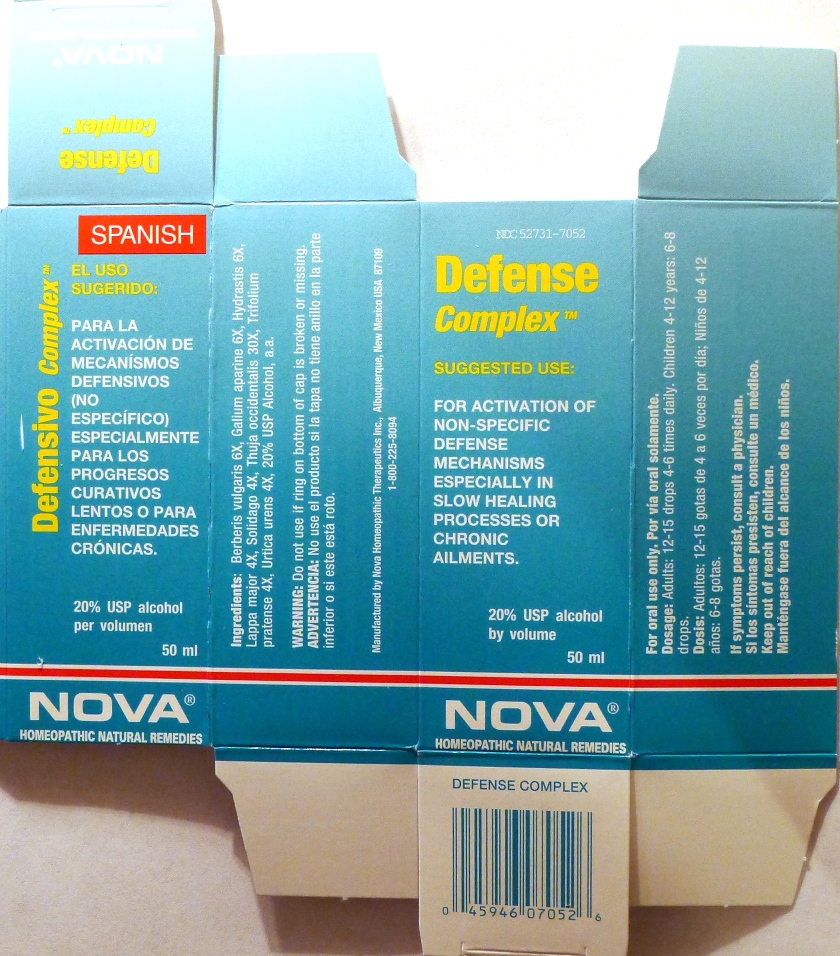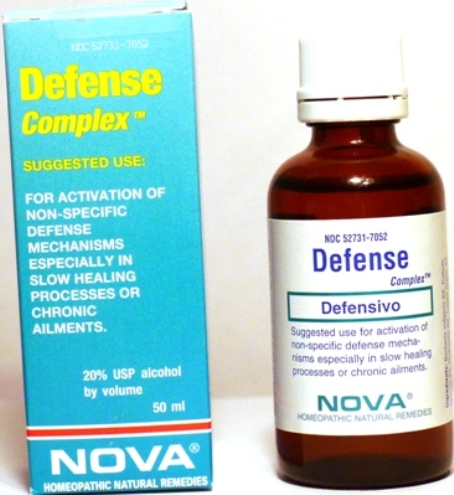 DRUG LABEL: Defense Complex
NDC: 52731-7052 | Form: LIQUID
Manufacturer: Nova Homeopathic Therapeutics, Inc.
Category: homeopathic | Type: HUMAN OTC DRUG LABEL
Date: 20110601

ACTIVE INGREDIENTS: BERBERIS VULGARIS ROOT BARK 6 [hp_X]/1 mL; GALIUM APARINE 6 [hp_X]/1 mL; GOLDENSEAL 6 [hp_X]/1 mL; SOLIDAGO VIRGAUREA FLOWERING TOP 4 [hp_X]/1 mL; TRIFOLIUM PRATENSE FLOWER 4 [hp_X]/1 mL; THUJA OCCIDENTALIS LEAFY TWIG 30 [hp_X]/1 mL; URTICA URENS 4 [hp_X]/1 mL
INACTIVE INGREDIENTS: ALCOHOL

Defense Complex

Purpose:

Suggested use for one or more of the following symptoms:

For activation of non-specific defense mechanisms especially in slow healing processes or chronic ailments.

Usage and Dosage:

For oral use only.

DOSAGE AND ADMINISTRATION

Adults:
In Acute Phase:
12-15 drops, every half hour until relief occurs
When Relief Occurs:
12-15 drops, 4-6 times per day
Children 4-12 years:
6-8 drops, 4-6 times per day

Warnings:

Keep out of reach of children.

WARNINGS

If symptoms persist, consult a physician.
Do not use if ring on bottom of cap is broken or missing.

Active Ingredients:

Berberis vulgaris 6X, Galium aparine 6X, Hydrastis 6X, Lappa major 4X, Solidago 4X, Thuja occidentalis 30X, Trifolium pratense 4X, Urtica urens 4X

Inactive Ingredients:

Alcohol, 20% USP

QUESTIONS

Manufactured by Nova Homeopathic Therapeutics Inc., Albuquerque, New Mexico USA 87109
1-800-225-8094

PACKAGE LABEL

Defense Complex Product

Defense Complex Bottle Label

Defense Complex Box